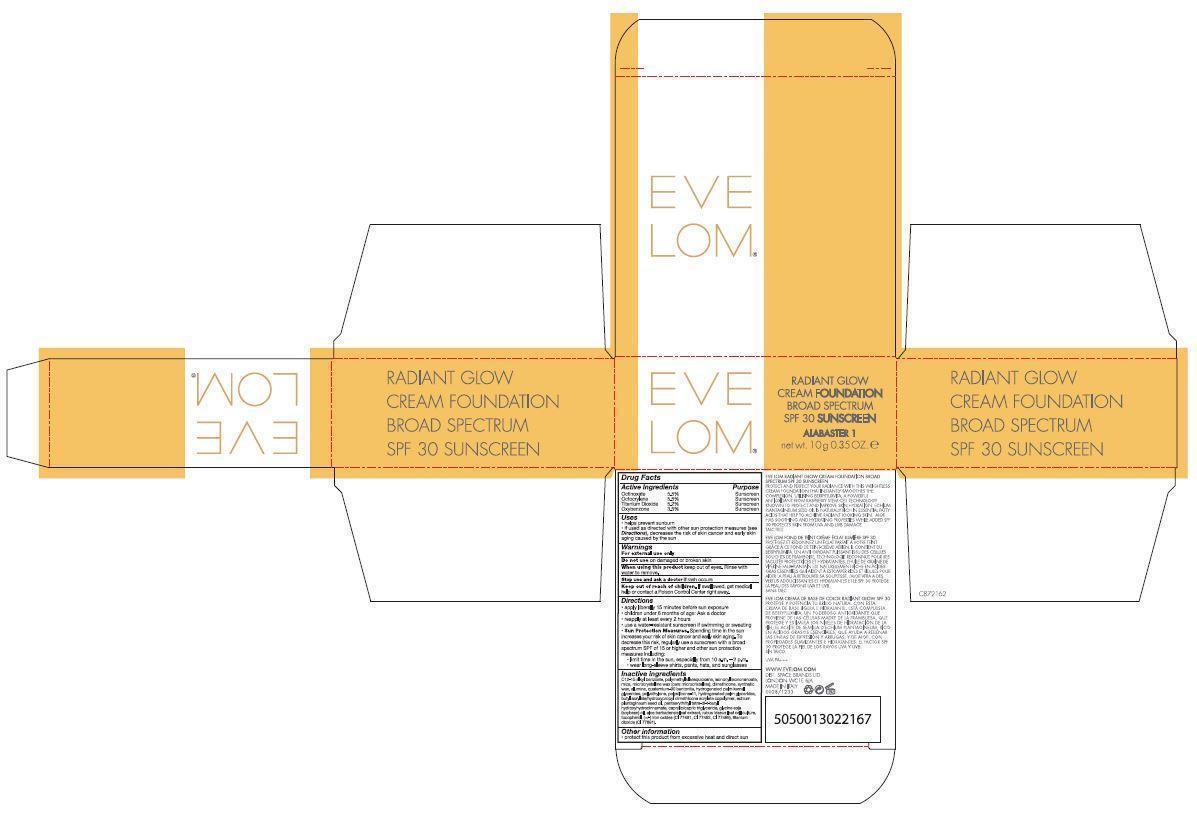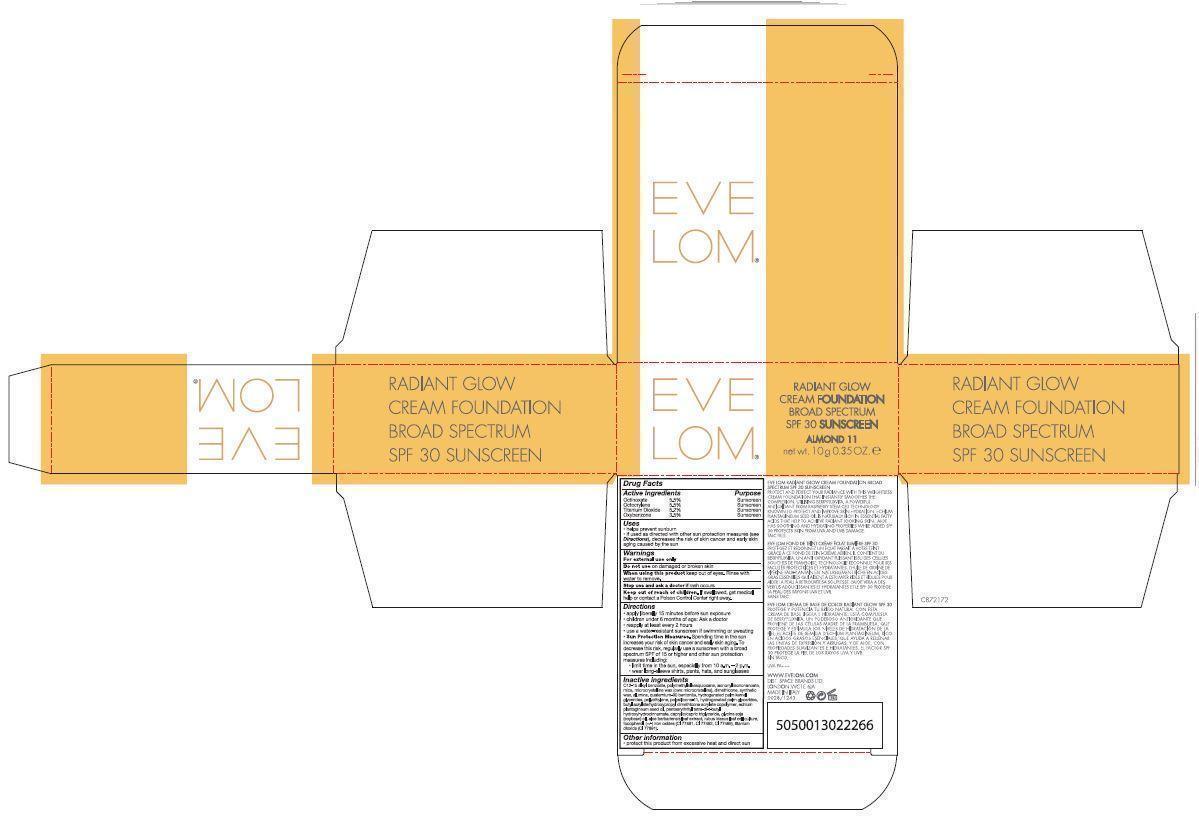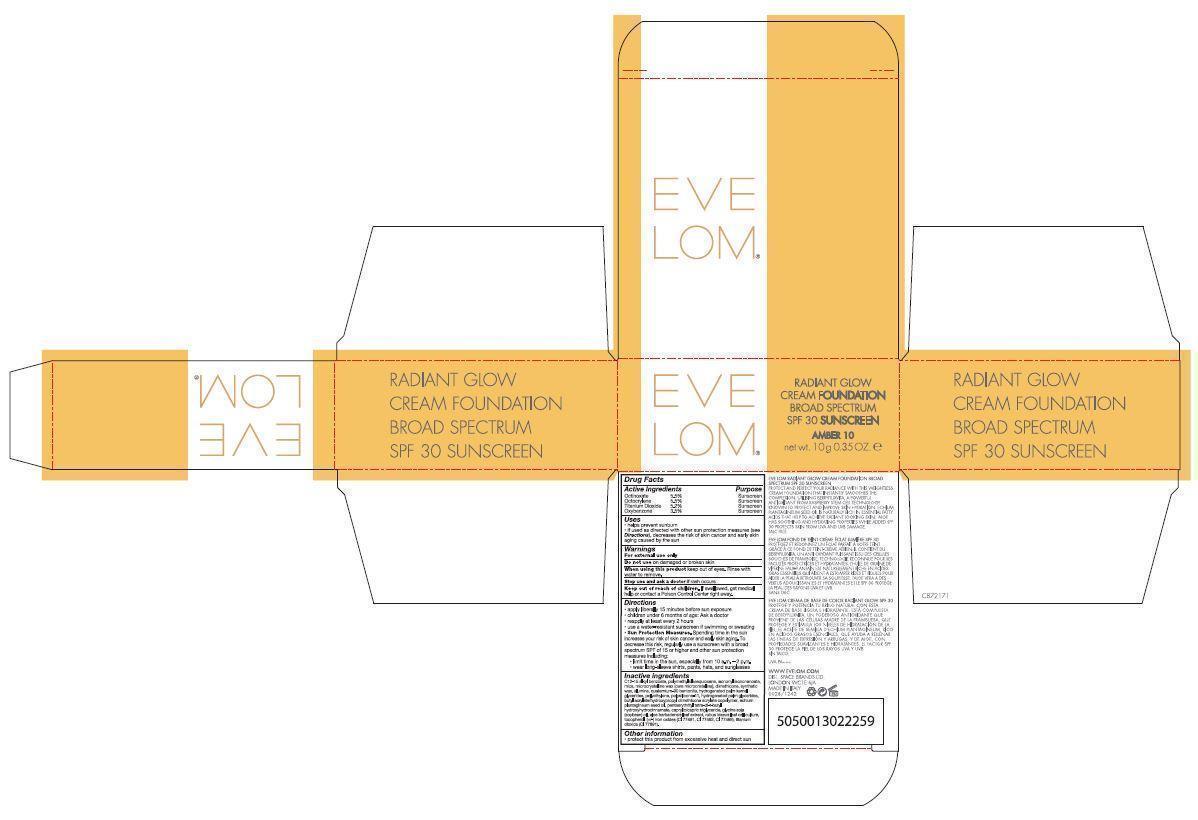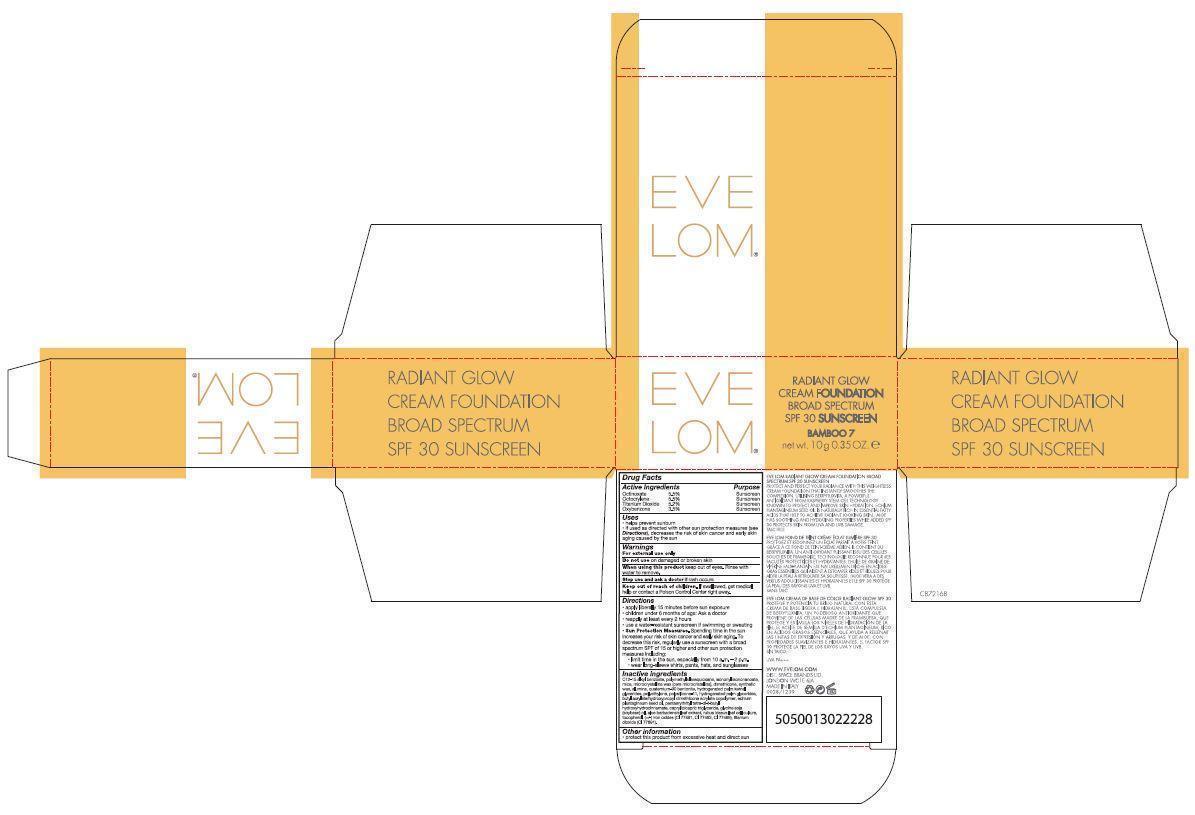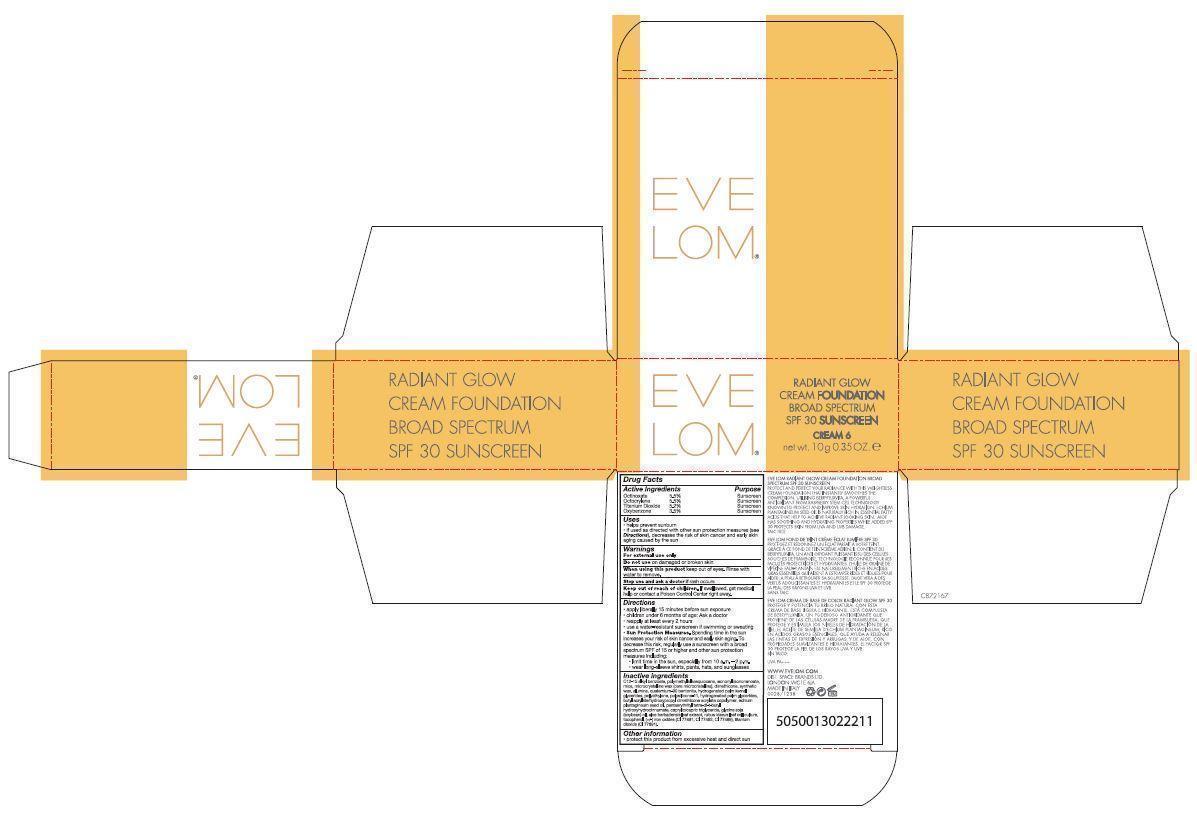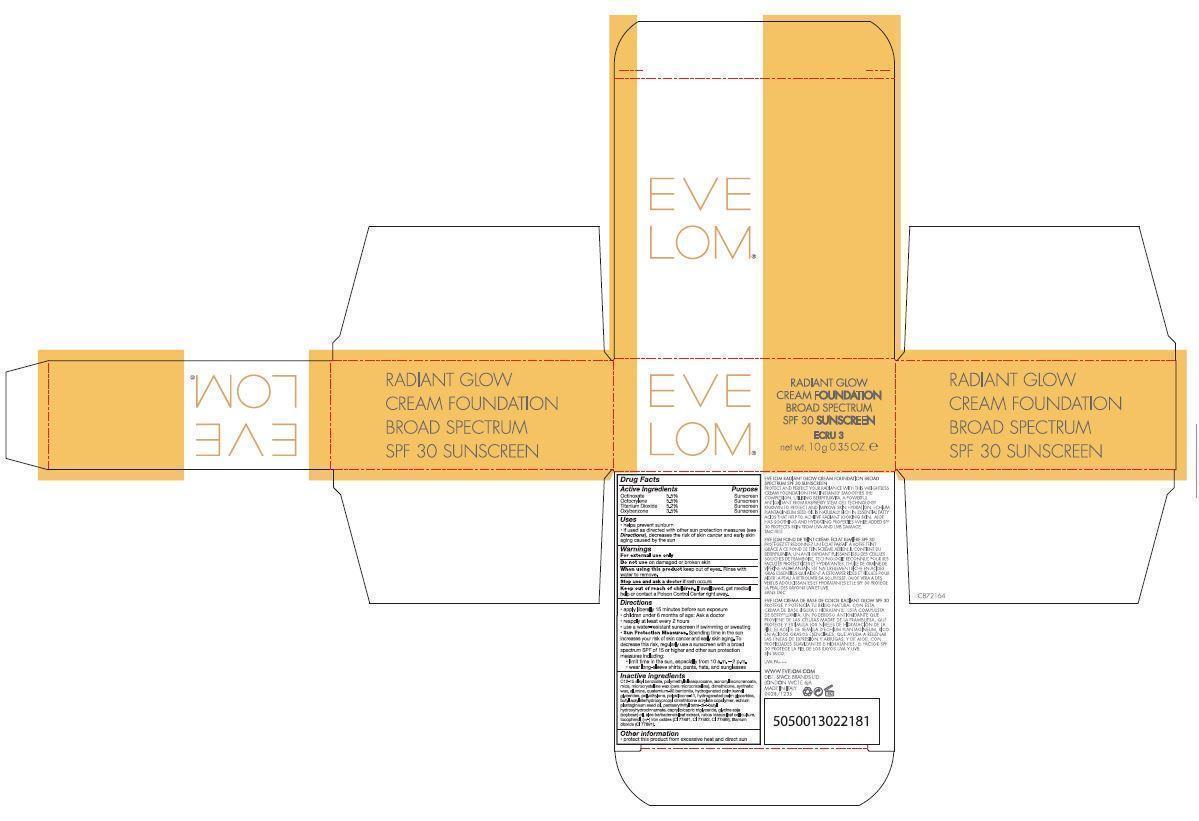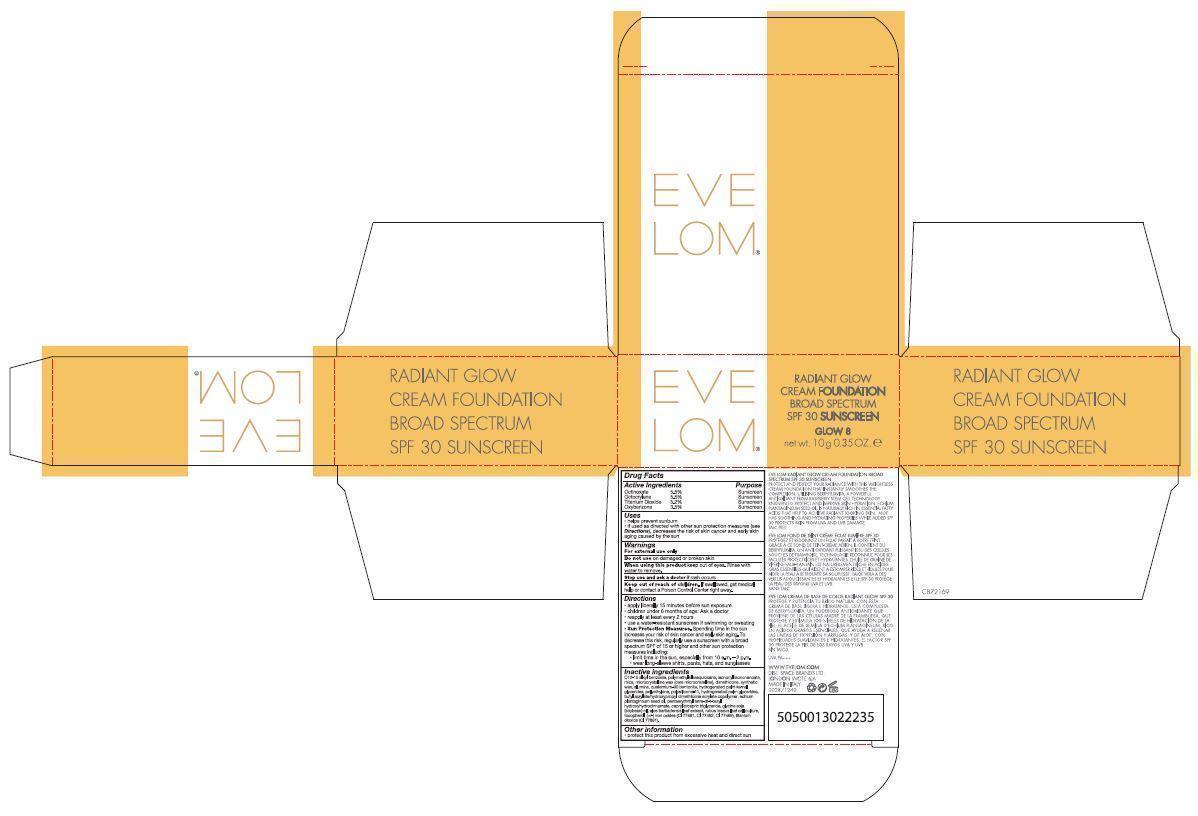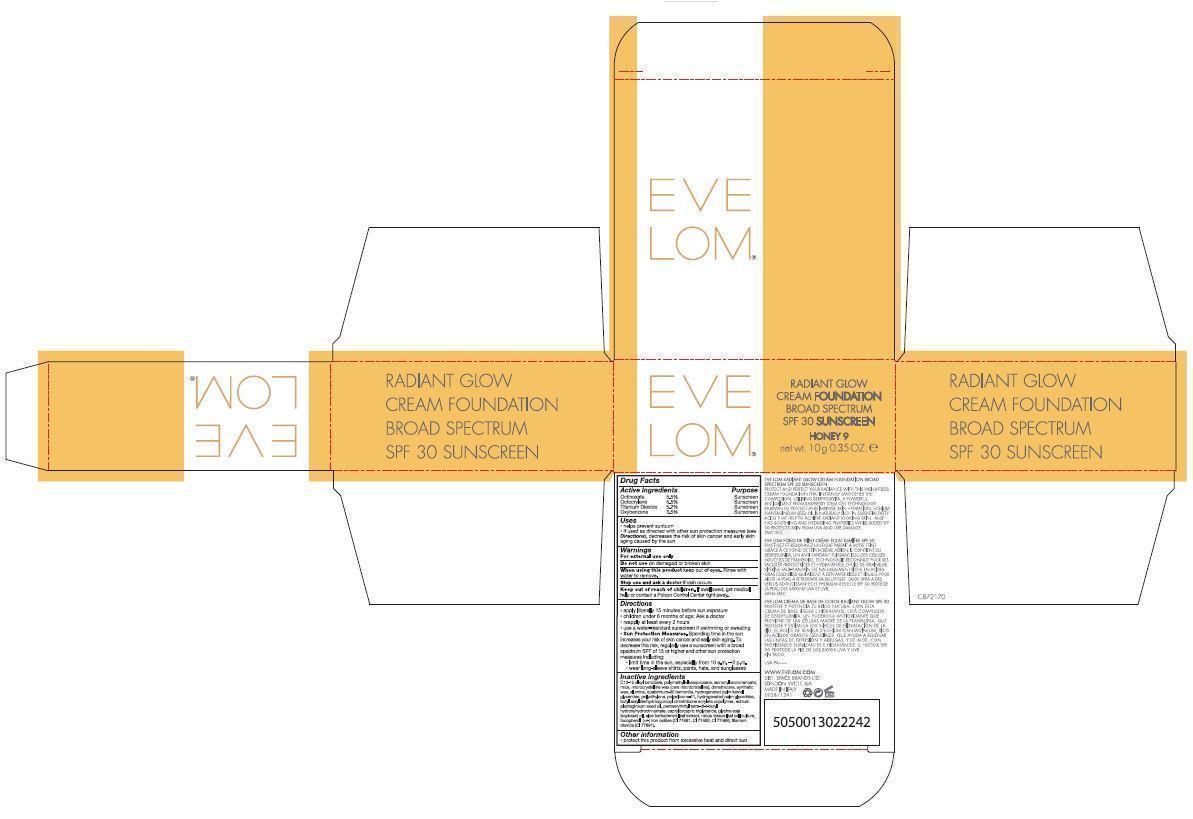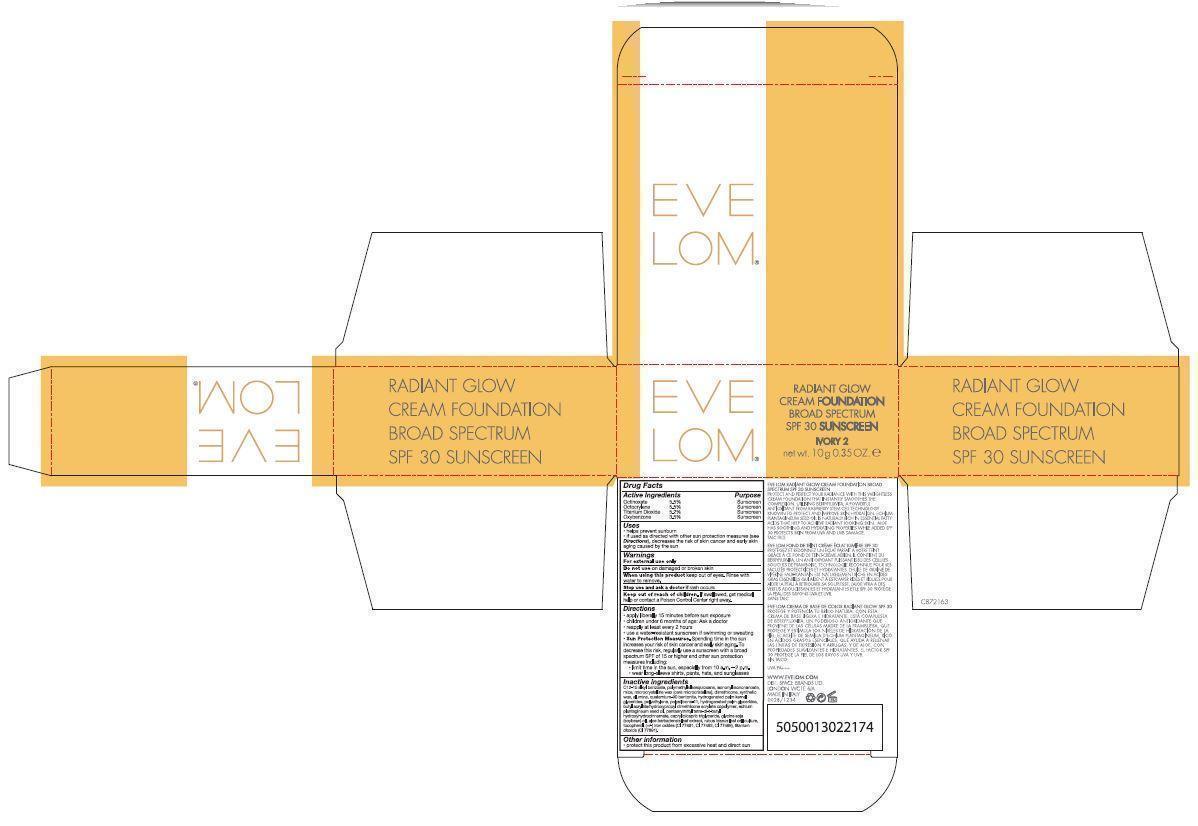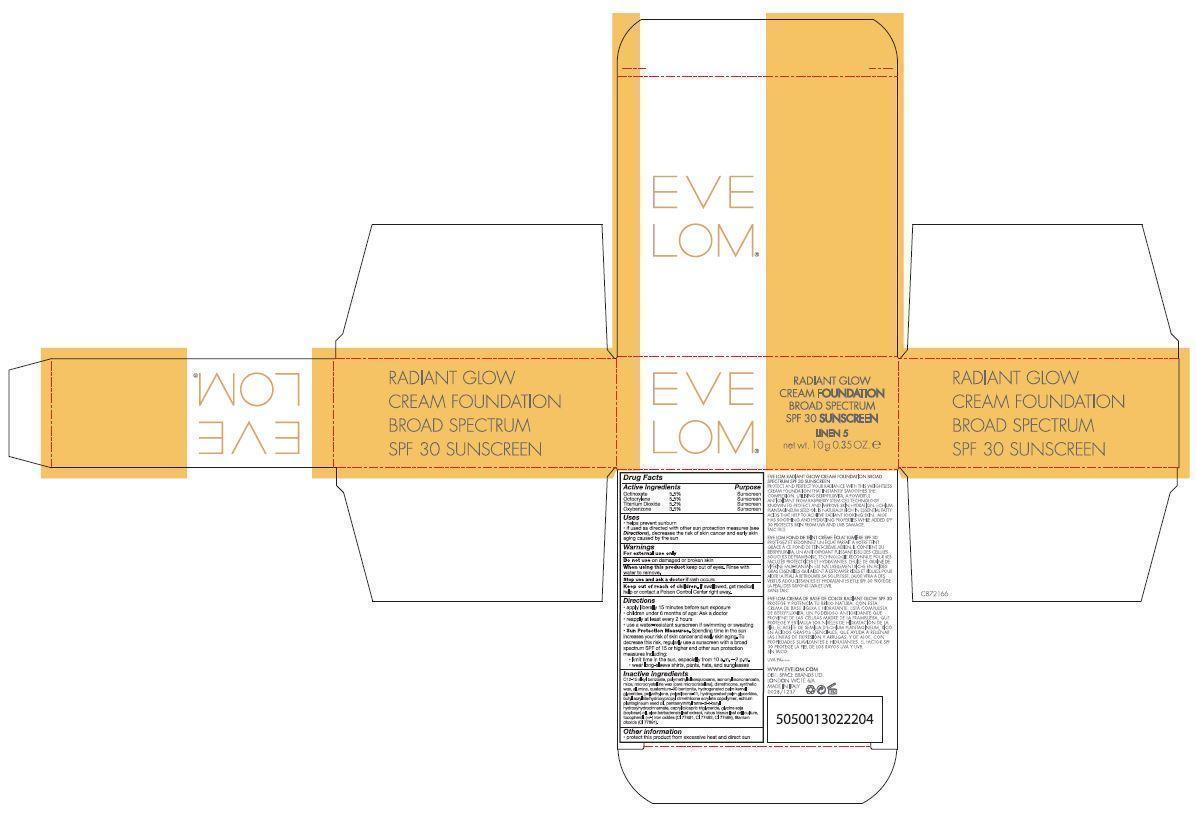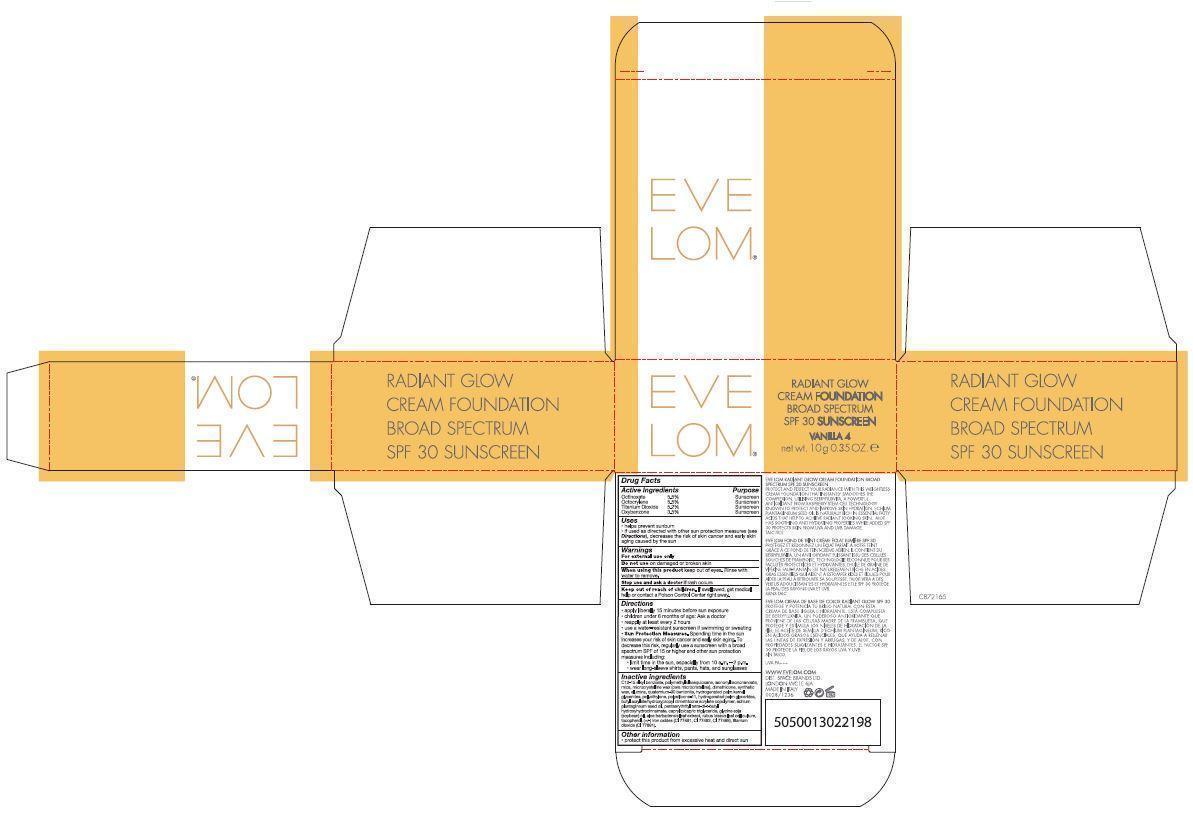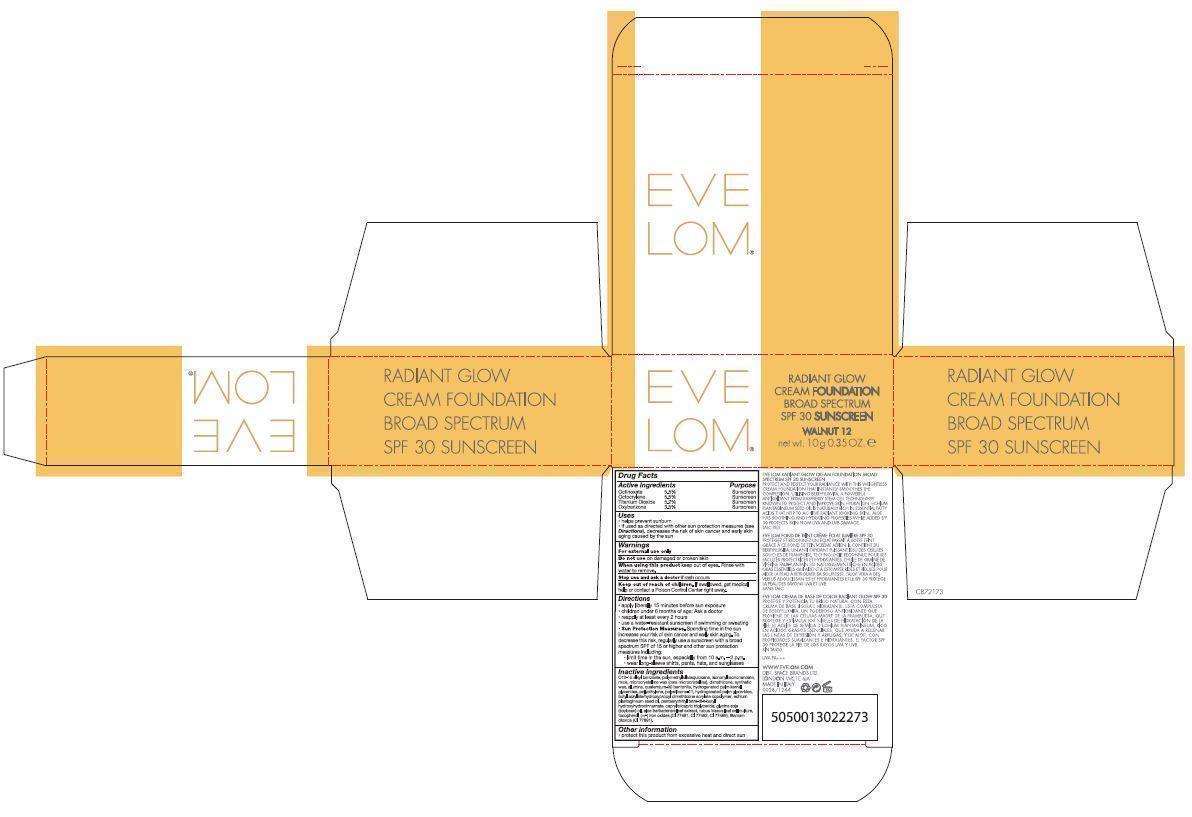 DRUG LABEL: Eve Lom Radiant Glow Cream Foundation Broad Spectrum SPF 30 Sunscreen
NDC: 61601-1244 | Form: CREAM
Manufacturer: Space Brands Limited
Category: otc | Type: HUMAN OTC DRUG LABEL
Date: 20141022

ACTIVE INGREDIENTS: OCTINOXATE 0.55 g/10 g; OCTOCRYLENE 0.55 g/10 g; TITANIUM DIOXIDE 0.52 g/10 g; OXYBENZONE 0.35 g/10 g
INACTIVE INGREDIENTS: C12-15 ALKYL BENZOATE; POLYMETHYLSILSESQUIOXANE (11 MICRONS); ISONONYL ISONONANOATE; FERRIC OXIDE YELLOW; MICA; MICROCRYSTALLINE WAX; DIMETHICONE; SYNTHETIC WAX (1200 MW); ALUMINUM OXIDE; FERRIC OXIDE RED; HYDROGENATED PALM KERNEL GLYCERIDES; HIGH DENSITY POLYETHYLENE; FERROSOFERRIC OXIDE; HYDROGENATED PALM GLYCERIDES; ECHIUM PLANTAGINEUM SEED OIL; PENTAERYTHRITOL TETRAKIS(3-(3,5-DI-TERT-BUTYL-4-HYDROXYPHENYL)PROPIONATE); MEDIUM-CHAIN TRIGLYCERIDES; SOYBEAN OIL; ALOE VERA LEAF; TOCOPHEROL

Eve Lom® Radiant Glow Cream Foundation Broad Spectrum SPF 30 Sunscreen

Drug Facts

Active Ingredients Purpose

Octinoxate Sunscreen

Octocrylene Sunscreen

Titanium Dioxide Sunscreen

Oxybenzone Sunscreen

Uses

- helps prevent sunburn
- if used as directed with other sun protection measures (see Directions), decreases the risk of skin cancer and early skin aging caused by the sun

Warnings

For external use only

Do not use on damaged or broken skin

When using this product keep out of eyes. Rinse with water to remove.

Stop use and ask a doctor if rash occurs.

Keep out of reach of children.

If swallowed, get medical help or contact a Poison Control Center right away.

DOSAGE AND ADMINISTRATION

- apply liberally 15 minutes before sun exposure
- children under 6 months of age: Ask a doctor
- reapply at least every 2 hours
- use a water-resistant sunscreen if swimming or sweating
- Sun Protection Measures. Spending time in the sun incrteases your risk of skin cancer and early skin aging. To decrease this risk, regularly use a sunscreen with a broad spectrum SPF of 15 or higher and other sun protection measures including:

- limit time in the sun, especially from 10 a.m. - 2 p.m.

- wear long-sleeve shirts, pants, hats, and sunglasses

Inactive ingredients

C12-15 alkyl benzoate, polymethylsilsesquioxane, isononyl isononanoate, mica, microcrystalline wax (cera microcristallina), dimethicone, synthetic wax, alumina, quaternium-90 bentonite, hydrogenated palm kernel glycerides, polyethylene, polysilicone-11, hydrogenated palm glycerides, butyl acrylate/hydroxypropyl dimethicone acrylate copolymer, echium plantagineum seed oil, pentaerythrityl tetra-di-t-butyl hydroxyhydrocinnamate, caprylic/capric triglyceride, glycine soja (soybean) oil, aloe barbadensis leaf extract, rubus idaeus leaf cell culture, tocopherol, iron oxides (CI 77491, CI 77492, CI 77499), titanium dioxide (CI 77891).

Other information

- protect this product from excessive heat and direct sun